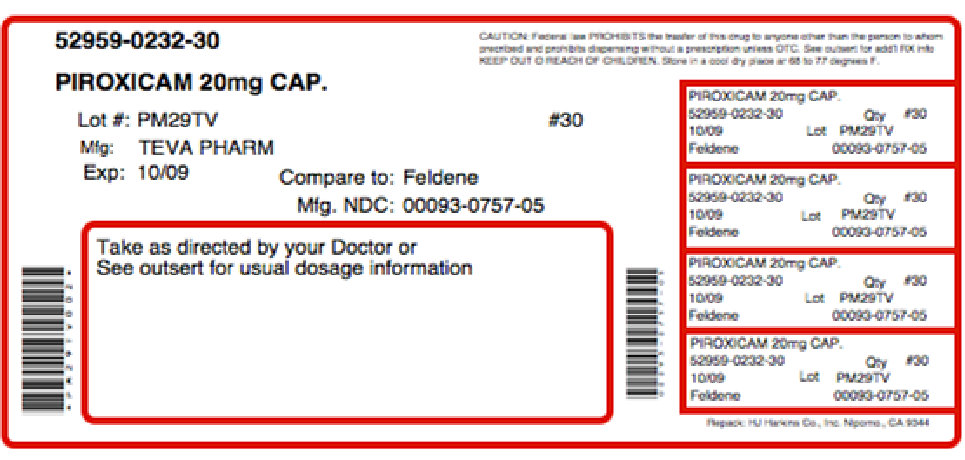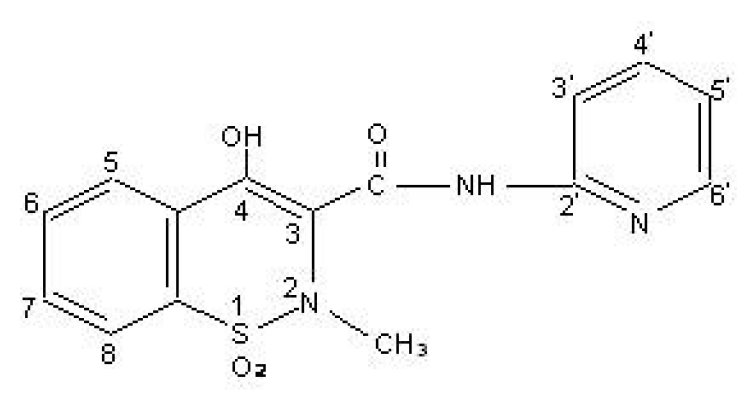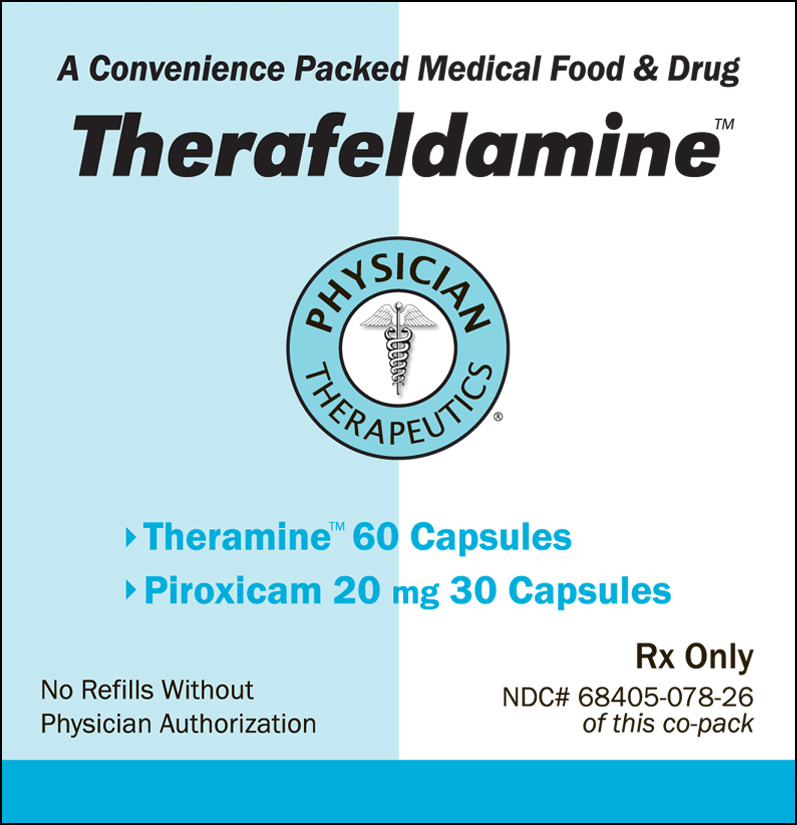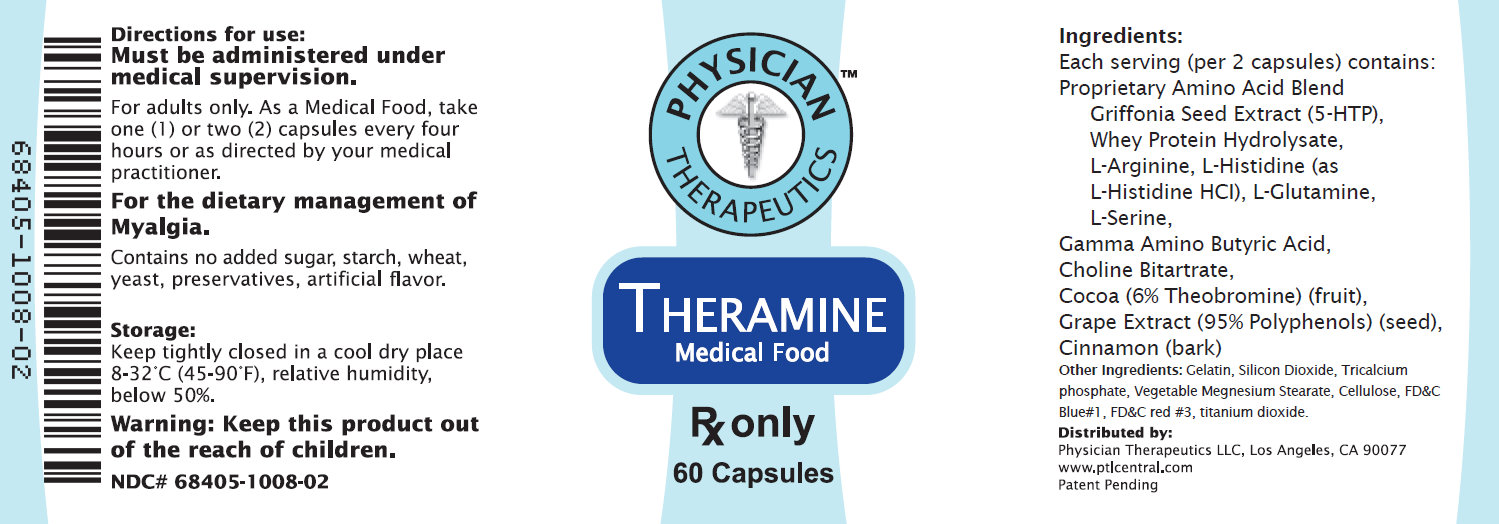 DRUG LABEL: Therafeldamine
NDC: 68405-078 | Form: KIT | Route: ORAL
Manufacturer: Physician Therapeutics LLC
Category: prescription | Type: HUMAN PRESCRIPTION DRUG LABEL
Date: 20110801

ACTIVE INGREDIENTS: PIROXICAM 20 mg/1 1; .GAMMA.-AMINOBUTYRIC ACID 100 mg/1 1
INACTIVE INGREDIENTS: SILICON DIOXIDE; STARCH, CORN; D&C YELLOW NO. 10; FD&C GREEN NO. 3; GELATIN; LACTOSE; MAGNESIUM STEARATE; POVIDONE; SODIUM LAURYL SULFATE; TITANIUM DIOXIDE; MAGNESIUM STEARATE; CELLULOSE, MICROCRYSTALLINE; MALTODEXTRIN; GELATIN


Therafeldamine

BOXED WARNING

For Oral Use

Cardiovascular Risk
• NSAIDs may cause an increased risk of serious cardiovascular thrombotic events, myocardial infarction, and stroke,
which can be fatal. This risk may increase with duration of use. Patients with cardiovascular disease or risk factors for
cardiovascular disease may be at greater risk (see WARNINGS).

• Piroxicam® is contraindicated for the treatment of peri-operative pain in the setting of coronary artery bypass graft
(CABG) surgery (see WARNINGS).

Gastrointestinal Risk
• NSAIDs cause an increased risk of serious gastrointestinal adverse events including bleeding, ulceration, and perforation of
the stomach or intestines, which can be fatal. These events can occur at any time during use and without warning symptoms.
Elderly patients are at greater risk for serious gastrointestinal events (see WARNINGS).

DESCRIPTION
Piroxicam® contains piroxicam which is a member of the oxicam group of nonsteroidal anti-inflammatory drugs (NSAIDs). Each maroon and blue capsule contains 10 mg piroxicam, each maroon capsule contains 20 mg piroxicam for oral administration. The chemical name for piroxicam is 4-hydroxyl-2-methyl-N-2-pyridinyl-2H-1,2,-benzothiazine-3-carboxamide 1,1-dioxide. Piroxicam occurs as a white crystalline solid, sparingly soluble in water, dilute acid, and most organic solvents. It is slightly soluble in alcohol and in aqueous solutions. It exhibits a weakly acidic 4-hydroxy proton (pKa 5.1) and a weakly basic pyridyl nitrogen (pKa 1.8). The molecular weight of piroxicam is 331.35. Its molecular formula is C15H13N3O4S and it has the following structural formula:

The inactive ingredients in Piroxicam capsules include: Blue 1, Red 3, lactose, magnesium stearate, sodium lauryl sulfate, starch.

PHARMACODYNAMICS

CLINICAL PHARMACOLOGY

Pharmacodynamics
Piroxicam is a nonsteroidal anti-inflammatory drug (NSAID) that exhibits anti-inflammatory, analgesic, and antipyretic activities in animal models. The mechanism of action of Piroxicam, like that of other NSAIDs, is not completely understood but may be related to prostaglandin synthetase inhibition.

Pharmacokinetics

Absorption
Piroxicam is well absorbed following oral administration. Drug plasma concentrations are proportional for 10 and 20 mg doses and generally peak within three to five hours after medication. The prolonged half-life (50 hours) results in the maintenance of relatively stable plasma concentrations throughout the day on once daily doses and to significant accumulation upon multiple dosing. A single 20 mg dose generally produces peak piroxicam plasma levels of 1.5 to 2 mcg/mL, while maximum drug plasma concentrations, after repeated daily ingestion of 20 mg Piroxicam, usually stabilize at 3–8 mcg/mL. Most patients approximate steady state plasma levels within 7–12 days. Higher levels, which approximate steady state at two to three weeks, have been observed in patients in whom longer plasma half-lives of piroxicam occurred.

With food there is a slight delay in the rate but not the extent of absorption following oral administration. The concomitant administration of antacids (aluminum hydroxide or aluminum hydroxide with magnesium hydroxide) have been shown to have no effect on the plasma levels of orally administered piroxicam.

Distribution
The apparent volume of distribution of piroxicam is approximately 0.14 L/kg. Ninety-nine percent of plasma piroxicam is bound to plasma proteins. Piroxicam is excreted into human milk. The presence in breast milk has been determined during initial and longterm conditions (52 days). Piroxicam appeared in breast milk at about 1% to 3% of the maternal concentration. No accumulation of piroxicam occurred in milk relative to that in plasma during treatment.

Metabolism
Metabolism of piroxicam occurs by hydroxylation at the 5 position of the pyridyl side chain and conjugation of this product; by cyclodehydration; and by a sequence of reactions involving hydrolysis of the amide linkage, decarboxylation, ring contraction, and N-demethylation. In vitro studies indicate cytochrome P4502C9 (CYP2C9) as the main enzyme involved in the formation to the 5'-hydroxy-piroxicam, the major metabolite (see Pharmacogenetics, and Special Populations, Poor Metabolizers of CYP2C9 Substrates). The biotransformation products of piroxicam metabolism are reported to not have any anti-inflammatory activity.

Higher systemic exposure of piroxicam has been noted in subjects with CYP2C9 polymorphisms compared to normal metabolizer type subjects (see Pharmacogenetics, and Special Populations, Poor Metabolizers of CYP2C9 Substrates).

Excretion
Piroxicam and its biotransformation products are excreted in urine and feces, with about twice as much appearing in the urine as in the feces. Approximately 5% of a Piroxicam dose is excreted unchanged. The plasma half-life (T½) for piroxicam is approximately 50 hours.

Pharmacogenetics
CYP2C9 activity is reduced in individuals with genetic polymorphisms, such as the CYP2C9*2 and CYP2C9*3 polymorphisms. Limited data from one published report that included nine subjects each with heterozygous CYP2C9*1/*2 and CYP2C9*1/*3 genotypes and one subject with the homozygous CYP2C9*3/*3 genotype showed piroxicam systemic levels that were 1.7-, 1.7- and 5.3-fold, respectively, higher compared to the 17 subjects with CYP2C9*1/*1 or normal metabolizer genotype. The pharmacokinetics of piroxicam have not been evaluated in subjects with other CYP2C9 polymorphisms, such as *5, *6, *9 and *11. It is estimated that the frequency of the homozygous *3/*3 genotype is 0.3% to 1.0% in various ethnic groups.

Special Populations

Pediatric
Piroxicam has not been investigated in pediatric patients.

Race
Pharmacokinetic differences due to race have not been identified.

Hepatic Insufficiency
The effects of hepatic disease on Piroxicam pharmacokinetics have not been established. However, a substantial portion of Piroxicam elimination occurs by hepatic metabolism. Consequently, patients with hepatic disease may require reduced doses of Piroxicam as compared to patients with normal hepatic function.

Poor Metabolizers of CYP2C9 Substrates
Patients who are known or suspected to be poor CYP2C9 metabolizers based on genotype or previous history/experience with other CYP2C9 substrates (such as warfarin and phenytoin) should be administered piroxicam with caution as they may have abnormally high plasma levels due to reduced metabolic clearance.

Renal Insufficiency
Piroxicam pharmacokinetics have been investigated in patients with renal insufficiency. Studies indicate patients with mild to moderate renal impairment may not require dosing adjustments. However, the pharmacokinetic properties of Piroxicam in patients with severe renal insufficiency or those receiving hemodialysis are not known.

Other Information
In controlled clinical trials, the effectiveness of Piroxicam has been established for both acute exacerbations and long-term management of rheumatoid arthritis and osteoarthritis. The therapeutic effects of Piroxicam are evident early in the treatment of both diseases with a progressive increase in response over several (8–12) weeks. Efficacy is seen in terms of pain relief and, when present, subsidence of inflammation. Doses of 20 mg/day Piroxicam display a therapeutic effect comparable to therapeutic doses of aspirin, with a lower incidence of minor gastrointestinal effects and tinnitus. Piroxicam has been administered concomitantly with fixed doses of gold and corticosteroids. The existence of a "steroid-sparing" effect has not been adequately studied to date.

INDICATIONS AND USAGE
Carefully consider the potential benefits and risks of Piroxicam and other treatment options before deciding to use Piroxicam. Use the lowest effective dose for the shortest duration consistent with individual patient treatment goals (see WARNINGS).
Piroxicam is indicated:
• For relief of the signs and symptoms of osteoarthritis.
• For relief of the signs and symptoms of rheumatoid arthritis.

CONTRAINDICATIONS
Piroxicam is contraindicated in patients with known hypersensitivity to piroxicam. Piroxicam should not be given to patients who have experienced asthma, urticaria, or allergic-type reactions after taking aspirin or other NSAIDs. Severe, rarely fatal, anaphylactic-like reactions to NSAIDs have been reported in such patients (see WARNINGS: Anaphylactoid Reactions and PRECAUTIONS: Preexisting Asthma). Piroxicam is contraindicated for the treatment of peri-operative pain in the setting of coronary artery bypass graft (CABG) surgery (see WARNINGS).

WARNINGS

CARDIOVASCULAR EFFECTS

Cardiovascular Thrombotic Events
Clinical trials of several COX-2 selective and nonselective NSAIDs of up to three years duration have shown an increased risk of serious cardiovascular (CV) thrombotic events, myocardial infarction, and stroke, which can be fatal. All NSAIDs, both COX-2 selective and nonselective, may have a similar risk. Patients with known CV disease or risk factors for CV disease may be at greater risk. To minimize the potential risk for an adverse CV event in patients treated with an NSAID, the lowest effective dose should be used for the shortest duration possible. Physicians and patients should remain alert for the development of such events, even in the absence of previous CV symptoms. Patients should be informed about the signs and/or symptoms of serious CV events and the steps to take if they occur.

There is no consistent evidence that concurrent use of aspirin mitigates the increased risk of serious CV thrombotic events associated with NSAID use. The concurrent use of aspirin and an NSAID does increase the risk of serious GI events (see WARNINGS, Gastrointestinal Effects - Risk of Ulceration, Bleeding, and Perforation).

Two large, controlled clinical trials of a COX-2 selective NSAID for the treatment of pain in the first 10–14 days following CABG surgery found an increased incidence of myocardial infarction and stroke (see CONTRAINDICATIONS).

Hypertension
NSAIDs, including Piroxicam, can lead to onset of new hypertension or worsening of preexisting hypertension, either of which may contribute to the increased incidence of CV events. Patients taking thiazides or loop diuretics may have impaired response to these therapies when taking NSAIDs. NSAIDs, including Piroxicam, should be used with caution in patients with hypertension. Blood pressure (BP) should be monitored closely during the initiation of NSAID treatment and throughout the course of therapy.

Congestive Heart Failure and Edema
Fluid retention and edema have been observed in some patients taking NSAIDs. Piroxicam should be used with caution in patients with fluid retention or heart failure.

Gastrointestinal Effects - Risk of Ulceration, Bleeding, and Perforation
NSAIDs, including Piroxicam, can cause serious gastrointestinal (GI) adverse events including inflammation, bleeding, ulceration, and perforation of the stomach, small intestine, or large intestine, which can be fatal. These serious adverse events can occur at any time, with or without warning symptoms, in patients treated with NSAIDs. Only one in five patients who develop a serious upper GI adverse event on NSAID therapy is symptomatic. Upper GI ulcers, gross bleeding, or perforation caused by NSAIDs occur in approximately 1% of patients treated for 3–6 months, and in about 2–4% of patients treated for one year. These trends continue with longer duration of use, increasing the likelihood of developing a serious GI event at some time during the course of therapy. However, even short-term therapy is not without risk.
NSAIDs should be prescribed with extreme caution in those with a prior history of ulcer disease or gastrointestinal bleeding. Patients with a prior history of peptic ulcer disease and/or gastrointestinal bleeding who use NSAIDs have a greater than 10-fold increased risk for developing a GI bleed compared to patients with neither of these risk factors. Other factors that increase the risk of GI bleeding in patients treated with NSAIDs include concomitant use of oral corticosteroids or anticoagulants, longer duration of NSAID therapy, smoking, use of alcohol, older age, and poor general health status. Most spontaneous reports of fatal GI events are in elderly or debilitated patients and, therefore, special care should be taken in treating this population.
To minimize the potential risk for an adverse GI event in patients treated with an NSAID, the lowest effective dose should be used for the shortest possible duration. Patients and physicians should remain alert for signs and symptoms of GI ulcerations and bleeding during NSAID therapy and promptly initiate additional evaluation and treatment if a serious GI event is suspected. This should include discontinuation of the NSAID until a serious GI adverse event is ruled out. For high-risk patients, alternate therapies that do not involve NSAIDs should be considered.

Renal Effects
Long-term administration of NSAIDs has resulted in renal papillary necrosis and other renal injury. Renal toxicity has also been seen in patients in whom renal prostaglandins have a compensatory role in the maintenance of renal perfusion. In these patients, administration of a nonsteroidal anti-inflammatory drug may cause a dose-dependent reduction in prostaglandin formation and, secondarily, in renal blood flow, which may precipitate overt renal decompensation. Patients at greatest risk of this reaction are those with impaired renal function, heart failure, liver dysfunction, those taking diuretics and ACE-inhibitors, and the elderly. Discontinuation of NSAID therapy is usually followed by recovery to the pretreatment state.

Advanced Renal Disease
No information is available from controlled clinical studies regarding the use of Piroxicam in patients with advanced renal disease. Therefore, treatment with Piroxicam is not recommended in these patients with advanced renal disease. If Piroxicam therapy must be initiated, close monitoring of the patient's renal function is advisable.

Anaphylactoid Reactions
As with other NSAIDs, anaphylactoid reactions may occur in patients without known prior exposure to Piroxicam. Piroxicam should not be given to patients with the aspirin triad. This symptom complex typically occurs in asthmatic patients who experience rhinitis with or without nasal polyps, or who exhibit severe, potentially fatal bronchospasm after taking aspirin or other NSAIDs (see CONTRAINDICATIONS and PRECAUTIONS: Preexisting Asthma). Emergency help should be sought in cases where an anaphylactoid reaction occurs.

Skin Reactions
NSAIDs, including Piroxicam, can cause serious skin adverse events such as exfoliative dermatitis, Stevens-Johnson Syndrome (SJS), and toxic epidermal necrolysis (TEN), which can be fatal. These serious events may occur without warning. Patients should be informed about the signs and symptoms of serious skin manifestations and use of the drug should be discontinued at the first appearance of skin rash or any other sign of hypersensitivity.

Other Hypersensitivity Reactions
A combination of dermatological and/or allergic signs and symptoms suggestive of serum sickness have occasionally occurred in conjunction with the use of Piroxicam. These include arthralgias, pruritus, fever, fatigue, and rash including vesiculobullous reactions and exfoliative dermatitis.

Pregnancy
In late pregnancy, as with other NSAIDs, Piroxicam should be avoided because it may cause premature closure of the ductus arteriosus.

PRECAUTIONS
General
Piroxicam cannot be expected to substitute for corticosteroids or to treat corticosteroid insufficiency. Abrupt discontinuation of corticosteroids may lead to disease exacerbation. Patients on prolonged corticosteroid therapy should have their therapy tapered slowly if a decision is made to discontinue corticosteroids. The pharmacological activity of Piroxicam in reducing fever and inflammation may diminish the utility of these diagnostic signs in detecting complications of presumed noninfectious, painful conditions.

Hepatic Effects
Borderline elevations of one or more liver tests may occur in up to 15% of patients taking NSAIDs, including Piroxicam. These laboratory abnormalities may progress, may remain unchanged, or may be transient with continuing therapy. Notable elevations of ALT or AST (approximately three or more times the upper limit of normal) have been reported in approximately 1% of patients in clinical trials with NSAIDs. In addition, rare cases of severe hepatic reactions, including jaundice and fatal fulminant hepatitis, liver necrosis and hepatic failure, some of them with fatal outcomes have been reported. A patient with symptoms and/or signs suggesting liver dysfunction, or in whom an abnormal liver test has occurred, should be evaluated for evidence of the development of more severe hepatic reaction while on therapy with Piroxicam. If clinical signs and symptoms consistent with liver disease develop, or if systemic manifestations occur (e.g., eosinophilia, rash, etc.), Piroxicam should be discontinued (see ADVERSE REACTIONS).

Hematological Effects
Anemia is sometimes seen in patients receiving NSAIDs, including Piroxicam. This may be due to fluid retention, occult or gross GI blood loss, or an incompletely described effect upon erythropoiesis. Patients on long-term treatment with NSAIDs, including Piroxicam, should have their hemoglobin or hematocrit checked if they exhibit any signs or symptoms of anemia. NSAIDs inhibit platelet aggregation and have been shown to prolong bleeding time in some patients. Unlike aspirin, their effect on platelet function is quantitatively less, of shorter duration, and reversible. Patients receiving Piroxicam who may be adversely affected by alterations in platelet function, such as those with coagulation disorders or patients receiving anticoagulants, should be carefully monitored.

Ophthalmologic Effects
Because of reports of adverse eye findings with nonsteroidal anti-inflammatory agents, it is recommended that patients who develop visual complaints during treatment with Piroxicam have ophthalmic evaluations.

Preexisting Asthma
Patients with asthma may have aspirin-sensitive asthma. The use of aspirin in patients with aspirin-sensitive asthma has been associated with severe bronchospasm which can be fatal. Since cross-reactivity, including bronchospasm, between aspirin and other nonsteroidal anti-inflammatory drugs has been reported in such aspirin-sensitive patients, Piroxicam should not be administered to patients with this form of aspirin sensitivity and should be used with caution in patients with preexisting asthma.

Information for Patients
Patients should be informed of the following information before initiating therapy with an NSAID and periodically during the course of ongoing therapy. Patients should also be encouraged to read the NSAID Medication Guide that accompanies each prescription dispensed.
• Piroxicam, like other NSAIDs, may cause CV side effects, such as MI or stroke, which may result in hospitalization and even death. Although serious CV events can occur without warning symptoms, patients should be alert for the signs and symptoms of chest pain, shortness of breath, weakness, slurring of speech, and should ask for medical advice when observing any indicative signs or symptoms. Patients should be apprised of the importance of this follow-up (see WARNINGS, CARDIOVASCULAR EFFECTS).

• Piroxicam, like other NSAIDs, can cause GI discomfort and, rarely, serious GI side effects, such as ulcers and bleeding, which may result in hospitalization and even death. Although serious GI tract ulcerations and bleeding can occur without warning symptoms, patients should be alert for the signs and symptoms of ulcerations and bleeding, and should ask for medical advice when observing any indicative signs or symptoms including epigastric pain, dyspepsia, melena, and hematemesis. Patients should be apprised of the importance of this follow-up (see WARNINGS, Gastrointestinal Effects - Risk of Ulceration, Bleeding, and Perforation).

• Piroxicam, like other NSAIDs, can cause serious skin side effects such as exfoliative dermatitis, SJS and TEN, which may result in hospitalization and even death. Although serious skin reactions may occur without warning, patients should be alert for the signs and symptoms of skin rash and blisters, fever, or other signs of hypersensitivity such as itching, and should ask for medical advice when observing any indicative signs or symptoms. Patients should be advised to stop the drug immediately if they develop any type of rash and contact their physicians as soon as possible.

• Patients should promptly report signs or symptoms of unexplained weight gain or edema to their physicians.

• Patients should be informed of the warning signs and symptoms of hepatotoxicity (e.g., nausea, fatigue, lethargy, pruritus, jaundice, right upper quadrant tenderness, and "flu-like" symptoms). If these occur, patients should be instructed to stop therapy and seek immediate medical therapy.

• Patients should be informed of the signs of an anaphylactoid reaction (e.g., difficulty breathing, swelling of the face or throat). If these occur, patients should be instructed to seek immediate emergency help (see WARNINGS).

• In late pregnancy, as with other NSAIDs, Piroxicam should be avoided because it may cause premature closure of the ductus arteriosus.

Laboratory Tests
Because serious GI tract ulcerations and bleeding can occur without warning symptoms, physicians should monitor for signs and symptoms of GI bleeding. Patients on long term treatment with NSAIDs should have their CBC and a chemistry profile checked periodically. If clinical signs and symptoms consistent with liver or renal disease develop, systemic manifestations occur (e.g., eosinophilia, rash, etc.), or if abnormal liver tests persist or worsen, Piroxicam should be discontinued.

Drug Interactions

Highly Protein Bound Drugs
Piroxicam is highly protein bound and, therefore, might be expected to displace other protein bound drugs. Physicians should closely monitor patients for a change in dosage requirements when administering Piroxicam to patients on other highly protein bound drugs.

Aspirin
When Piroxicam is administered with aspirin, its protein binding is reduced, although the clearance of free Piroxicam is not altered. Plasma levels of piroxicam are depressed to approximately 80% of their normal values when Piroxicam is administered (20 mg/day) in conjunction with aspirin (3900 mg/day). The clinical significance of this interaction is not known; however, as with other NSAIDs, concomitant administration of piroxicam and aspirin is not generally recommended because of the potential for increased adverse effects.

Methotrexate
NSAIDs have been reported to competitively inhibit methotrexate accumulation in rabbit kidney slices. This may indicate that they could enhance the toxicity of methotrexate. Caution should be used when NSAIDs are administered concomitantly with methotrexate.

ACE-Inhibitors
Reports suggest that NSAIDs may diminish the antihypertensive effect of ACE-inhibitors. This interaction should be given consideration in patients taking NSAIDs concomitantly with ACE-inhibitors.

Diuretics
Clinical studies, as well as postmarketing observations, have shown that Piroxicam can reduce the natriuretic effect of furosemide and thiazides in some patients. This response has been attributed to inhibition of renal prostaglandin synthesis. During concomitant therapy with NSAIDs, the patient should be observed closely for signs of renal failure (see WARNINGS: Renal Effects), as well as to assure diuretic efficacy.

Lithium
NSAIDs have produced an elevation of plasma lithium levels and a reduction in renal lithium clearance. The mean minimum lithium concentration increased 15% and the renal clearance was decreased by approximately 20%. These effects have been attributed to inhibition of renal prostaglandin synthesis by the NSAID. Thus, when NSAIDs and lithium are administered concurrently, subjects should be observed carefully for signs of lithium toxicity.

Warfarin
The effects of warfarin and NSAIDs on GI bleeding are synergistic, such that users of both drugs together have a risk of serious GI bleeding higher than users of either drug alone.

Carcinogenesis, Mutagenesis, Impairment of Fertility
Subacute, acute, and chronic toxicity studies have been carried out in rats, mice, dogs, and monkeys. The pathology most often seen was that characteristically associated with the animal toxicology of anti-inflammatory agents: renal papillary necrosis (see PRECAUTIONS) and gastrointestinal lesions.
Reproductive studies revealed no impairment of fertility in animals.

Pregnancy

Teratogenic Effects

Pregnancy Category C
Reproductive studies conducted in rats and rabbits have not demonstrated evidence of developmental abnormalities. However, animal reproduction studies are not always predictive of human response. There are no adequate and well-controlled studies in pregnant women. Piroxicam is not recommended for use in pregnant women since safety has not been established in humans. Piroxicam should be used in pregnancy only if the potential benefit justifies the potential risk to the fetus.

Nonteratogenic Effects
Because of the known effects of nonsteroidal anti-inflammatory drugs on the fetal cardiovascular system (closure of ductus arteriosus), use during pregnancy (particularly late pregnancy) should be avoided. In animal studies of Piroxicam, gastrointestinal tract toxicity was increased in pregnant females in the last trimester of pregnancy compared to nonpregnant females or females in earlier trimesters of pregnancy.

Labor and Delivery
In rat studies with NSAIDs, as with other drugs known to inhibit prostaglandin synthesis, an increased incidence of dystocia, delayed parturition, and decreased pup survival occurred. The effects of Piroxicam on labor and delivery in pregnant women are unknown.

Nursing Mothers
Piroxicam is excreted into human milk. The presence in breast milk has been determined during initial and long-term conditions (52 days). Piroxicam appeared in breast milk at about 1% to 3% of the maternal concentration. No accumulation of piroxicam occurred in milk relative to that in plasma during treatment. Piroxicam is not recommended for use in nursing mothers.

Pediatric Use
Safety and effectiveness in pediatric patients have not been established.

Geriatric Use
As with any NSAID, caution should be exercised in treating the elderly (65 years and older). Most spontaneous reports of fatal GI events with NSAIDs are in the elderly or debilitated patients and, therefore, care should be taken in treating this population. In addition to a past history of ulcer disease, older age and poor general health status (among other factors) may increase the risk for GI bleeding. To minimize the potential risk of an adverse GI event, the lowest effective dose should be used for the shortest possible duration (see WARNINGS, Gastrointestinal Effects – Risk of Ulceration, Bleeding, and Perforation). As with all other NSAIDs, there is a risk of developing renal toxicity in patients in which renal prostaglandins have a compensatory role in maintenance of renal perfusion. Discontinuation of nonsteroidal anti-inflammatory drug therapy is usually followed by recovery to the pretreatment state (see Warnings: Renal Effects).
In general, dose selection for an elderly patient should be cautious, usually starting at the low end of the dosing range, reflecting a greater frequency of impaired drug elimination and of concomitant disease or other drug therapy.

ADVERSE REACTIONS
In patients taking Piroxicam or other NSAIDs, the most frequently reported adverse experiences occurring in approximately 1–10% of patients are:
Cardiovascular System: Edema.

Digestive System: Anorexia, abdominal pain, constipation, diarrhea, dyspepsia, elevated liver enzymes, flatulence, gross bleeding/perforation, heartburn, nausea, ulcers (gastric/duodenal), vomiting.

Hemic and Lymphatic System: Anemia, increased bleeding time.

Nervous System: Dizziness, headache.

Skin and Appendages: Pruritus, rash.

Special Senses: Tinnitus.

Urogenital System: Abnormal renal function.

Additional adverse experiences reported occasionally include:

Body As a Whole: Fever, infection, sepsis.

Cardiovascular System: Congestive heart failure, hypertension, tachycardia, syncope.

Digestive System: Dry mouth, esophagitis, gastritis, glossitis, hematemesis, hepatitis, jaundice, melena, rectal bleeding, stomatitis.

Hemic and Lymphatic System: Ecchymosis, eosinophilia, epistaxis, leukopenia, purpura, petechial rash, thrombocytopenia.

Metabolic and Nutritional: Weight changes.

Nervous System: Anxiety, asthenia, confusion, depression, dream abnormalities, drowsiness, insomnia, malaise, nervousness, paresthesia, somnolence, tremors, vertigo.

Respiratory System: Asthma, dyspnea.

Skin and Appendages: Alopecia, bruising, desquamation, erythema, photosensitivity, sweat.

Special Senses: Blurred vision.

Urogenital System: Cystitis, dysuria, hematuria, hyperkalemia, interstitial nephritis, nephrotic syndrome, oliguria/polyuria, proteinuria, renal failure.

Other adverse reactions which occur rarely are:
Body As a Whole: Anaphylactic reactions, appetite changes, death, flu-like syndrome, pain (colic), serum sickness.

Cardiovascular System: Arrhythmia, exacerbation of angina, hypotension, myocardial infarction, palpitations, vasculitis.

Digestive System: Eructation, liver failure, pancreatitis.

Hemic and Lymphatic System: Agranulocytosis, hemolytic anemia, aplastic anemia, lymphadenopathy, pancytopenia.

Hypersensitivity: Positive ANA.

Metabolic and Nutritional: Hyperglycemia, hypoglycemia.

Nervous System: Akathisia, convulsions, coma, hallucinations, meningitis, mood alterations.

Respiratory: Respiratory depression, pneumonia.

Skin and Appendages: Angioedema, toxic epidermal necrosis, erythema multiforme, exfoliative dermatitis, onycholysis, Stevens-Johnson Syndrome, urticaria, vesiculobullous reaction.

Special Senses: Conjunctivitis, hearing impairment, swollen eyes.

OVERDOSAGE
Symptoms following acute NSAID overdoses are usually limited to lethargy, drowsiness, nausea, vomiting, and epigastric pain, which are generally reversible with supportive care. Gastrointestinal bleeding can occur. Hypertension, acute renal failure, respiratory depression, and coma may occur, but are rare. Anaphylactoid reactions have been reported with therapeutic ingestion of NSAIDs, and may occur following an overdose. Patients should be managed by symptomatic and supportive care following an NSAID overdose. There are no specific antidotes. Emesis and/or activated charcoal (60–100 g in adults, 1–2 g/kg in children) and/or osmotic cathartic may be indicated. The long plasma half-life of piroxicam should be considered when treating an overdose with piroxicam. Experiments in dogs have demonstrated that the use of multiple-dose treatments with activated charcoal could reduce the half-life of piroxicam by more than 50% and systemic bioavailability by as much as 37% when activated charcoal is given as late as 6 hours after ingestion of piroxicam. Forced diuresis, alkalinization of urine, hemodialysis, or hemoperfusion may not be useful due to high protein binding.

DOSAGE AND ADMINISTRATION
Carefully consider the potential benefits and risks of Piroxicam and other treatment options before deciding to use Piroxicam. Use the lowest effective dose for the shortest duration consistent with individual patient treatment goals (see WARNINGS). After observing the response to initial therapy with Piroxicam, the dose and frequency should be adjusted to suit an individual patient's needs.
For the relief of rheumatoid arthritis and osteoarthritis, the recommended dose is 20 mg given orally once per day. If desired, the daily dose may be divided. Because of the long half-life of Piroxicam, steady-state blood levels are not reached for 7–12 days. Therefore, although the therapeutic effects of Piroxicam are evident early in treatment, there is a progressive increase in response over several weeks and the effect of therapy should not be assessed for two weeks.

MEDICATION GUIDE

MEDICATION GUIDE FOR NON-STEROIDAL ANTI-INFLAMMATORY DRUGS (NSAIDS)
(See the end of this Medication Guide for a list of prescription NSAID medicines.)
What is the most important information I should know about medicines called Non-Steroidal Anti-Inflammatory Drugs (NSAIDs)?
NSAID medicines may increase the chance of a heart attack or stroke that can lead to death. This chance increases:
• with longer use of NSAID medicines

• in people who have heart disease

NSAID medicines should never be used right before or after a heart surgery called a "coronary artery bypass graft (CABG)."
NSAID medicines can cause ulcers and bleeding in the stomach and intestines at any time during treatment. Ulcers and bleeding:
• can happen without warning symptoms

• may cause death

The chance of a person getting an ulcer or bleeding increases with:
• taking medicines called "corticosteroids" and "anticoagulants"

• longer use

• smoking

• drinking alcohol

• older age

• having poor health

NSAID medicines should only be used:
• exactly as prescribed

• at the lowest dose possible for your treatment

• for the shortest time needed

What are Non-Steroidal Anti-Inflammatory Drugs (NSAIDs)?
NSAID medicines are used to treat pain and redness, swelling, and heat (inflammation) from medical conditions such as:
• different types of arthritis

• menstrual cramps and other types of short-term pain

Who should not take a Non-Steroidal Anti-Inflammatory Drug (NSAID)?
Do not take an NSAID medicine:
• if you had an asthma attack, hives, or other allergic reaction with aspirin or any other NSAID medicine

• for pain right before or after heart bypass surgery

Tell your healthcare provider:
• about all of your medical conditions.

• about all of the medicines you take. NSAIDs and some other medicines can interact with each other and cause serious side effects.
Keep a list of your medicines to show to your healthcare provider and pharmacist.

• if you are pregnant. NSAID medicines should not be used by pregnant women late in their pregnancy.

• if you are breastfeeding. Talk to your doctor.

What are the possible side effects of Non-Steroidal Anti-Inflammatory Drugs (NSAIDs)?
Serious side effects include:
• heart attack

• stroke

• high blood pressure

• heart failure from body swelling (fluid retention)

• kidney problems including kidney failure

• bleeding and ulcers in the stomach and intestine

• low red blood cells (anemia)

• life-threatening skin reactions

• life-threatening allergic reactions

• liver problems including liver failure

• asthma attacks in people who have asthma

Other side effects include:
• stomach pain

• constipation

• diarrhea

• gas

• heartburn

• nausea

• vomiting

• dizziness

Get emergency help right away if you have any of the following symptoms:
• shortness of breath or trouble breathing

• chest pain

• weakness in one part or side of your body

• slurred speech

• swelling of the face or throat

Stop your NSAID medicine and call your healthcare provider right away if you have any of the following symptoms:
• nausea

• more tired or weaker than usual

• itching

• your skin or eyes look yellow

• stomach pain

• flu-like symptoms

• vomit blood

• there is blood in your bowel movement or it is black and sticky like tar

• unusual weight gain

• skin rash or blisters with fever

• swelling of the arms and legs, hands and feet

These are not all the side effects with NSAID medicines. Talk to your healthcare provider or pharmacist for more information about NSAID medicines.
Call your doctor for medical advice about side effects. You may report side effects to FDA at 1-800-FDA-1088.
Other information about Non-Steroidal Anti-Inflammatory Drugs (NSAIDs)
• Aspirin is an NSAID medicine but it does not increase the chance of a heart attack. Aspirin can cause bleeding in the brain, stomach, and intestines. Aspirin can also cause ulcers in the stomach and intestines.

• Some of these NSAID medicines are sold in lower doses without a prescription (over –the –counter). Talk to your healthcare provider before using over –the –counter NSAIDs for more than 10 days.

NSAID medicines that need a prescription
Generic Name | Tradename
Celecoxib | Celebrex
Diclofenac | Cataflam, Voltaren, Arthrotec (combined with misoprostol)
Diflunisal | Dolobid
Etodolac | Lodine, Lodine XL
Fenoprofen | Nalfon, Nalfon 200
Flurbiprofen | Ansaid
Ibuprofen | Motrin, Tab-Profen, Vicoprofen* (combined with hydrocodone), Combunox (combined with oxycodone)
Indomethacin | Indocin, Indocin SR, Indo-Lemmon, Indomethagan
Ketoprofen | Oruvail
Ketorolac | Toradol
Mefenamic Acid | Ponstel
Meloxicam | Mobic
Nabumetone | Relafen
Naproxen | Naprosyn, Anaprox, Anaprox DS, EC-Naproxyn, Naprelan, Naprapac (copackaged with lansoprazole)
Oxaprozin | Daypro
Piroxicam | Piroxicam
Sulindac | Clinoril
Tolmetin | Tolectin, Tolectin DS, Tolectin 600

*Vicoprofen contains the same dose of ibuprofen as over-the-counter (OTC) NSAIDs, and is usually used for less than 10 days to treat pain. The OTC NSAID label warns that long term continuous use may increase the risk of heart attack or stroke.
This Medication Guide has been approved by the U.S. Food and Drug Administration

HOW SUPPLIED

Call your doctor for medical advice about side effects. You may report side effects to FDA at 1-800-FDA-1088.
This Medication Guide has been approved by the U.S. Food and Drug Administration.
Manufactured In Israel By:
TEVA PHARMACEUTICAL IND. LTD.
Jerusalem, 91010, Israel
Manufactured For:
TEVA PHARMACEUTICALS USA
Sellersville, PA 18960
Rev. B 7/2009
PRINCIPAL DISPLAY PANEL
Piroxicam Capsules USP 10 mg 100s Label Text
NDC 0093-0756-01
PIROXICAM
Capsules USP
10 mg
Each capsule contains:
piroxicam, USP 10 mg
ATTENTION PHARMACIST: Each patient is
required to receive a Medication Guide.
Rx only
100 CAPSULES
TEVA
PRINCIPAL DISPLAY PANEL
Piroxicam Capsules USP 20 mg 100s Label Text
NDC 0093-0757-01
PIROXICAM
Capsules USP
20 mg
Each capsule contains:
piroxicam, USP 20 mg
ATTENTION PHARMACIST: Each patient is
required to receive a Medication Guide.
Rx only
100 CAPSULES
TEVA

Theramine™ PRODUCT INFORMATION Theramine (U.S. patent pending) capsules by oral administration. A specially formulated Medical Food product, consisting of a proprietary blend of amino acids and polyphenol ingredients in specific proportions, for the dietary management of the metabolic processes associated with pain disorders and inflammatory conditions. (PD) (IC). Must be administered under physician supervision. Medical Foods Medical Food products are often used in hospitals (e.g., for burn victims or kidney dialysis patients) and outside of a hospital setting under a physician’s care for the dietary management of diseases in patients with particular medical or metabolic needs due to their disease or condition. Congress defined "Medical Food" in the Orphan Drug Act and Amendments of 1988 as "a food which is formulated to be consumed or administered enterally [or orally] under the supervision of a physician and which is intended for the specific dietary management of a disease or condition for which distinctive nutritional requirements, based on recognized scientific principles, are established by medical evaluation." Medical Foods are complex formulated products, requiring sophisticated and exacting technology. Theramine has been developed, manufactured, and labeled in accordance with both the statutory and the FDA regulatory definition of a Medical Food. Theramine must be used while the patient is under the ongoing care of a physician. PAIN DISORDERS (PD) INFLAMMATORY CONDITIONS (IC) PD and IC as a Metabolic Deficiency Disease A critical component of the definition of a Medical Food is the requirement for a distinctive nutritional deficiency. FDA scientists have proposed a physiologic definition of a distinctive nutritional deficiency as follows: “the dietary management of patients with specific diseases requires, in some instances, the ability to meet nutritional requirements that differ substantially from the needs of healthy persons. For example, in establishing the recommended dietary allowances for general, healthy population, the Food and Nutrition Board of the Institute of Medicine National Academy of Sciences, recognized that different or distinctive physiologic requirements may exist for certain persons with "special nutritional needs arising from metabolic disorders, chronic diseases, injuries, premature birth, other medical conditions and drug therapies. Thus, the distinctive nutritional needs associated with a disease reflects the total amount needed by a healthy person to support life or maintain homeostasis, adjusted for the distinctive changes in the nutritional needs of the patient as a result of the effects of the disease process on absorption, metabolism and excretion.” It was also proposed that in patients with certain disease states who respond to nutritional therapies, a physiologic deficiency of the nutrient is assumed to exist. For example, if a patient with pain disorders responds to a tryptophan formulation by decreasing perceived pain, a deficiency of tryptophan is assumed to exist. Patients with pain disorders and inflammatory conditions are known to have nutritional deficiencies of tryptophan, choline, arginine, GABA, flavonoids, and certain antioxidants. Patients with pain disorders and inflammatory conditions frequently exhibit reduced plasma levels of tryptophan and GABA and have been shown to respond to oral administration of GABA, arginine, tryptophan, or a 5-hydoxytryptophan formulation. Research has shown that tryptophan, arginine or GABA reduced diets result in a fall of circulating tryptophan, arginine, and/or GABA. Patients with pain disorders frequently exhibit activation of the degradation pathways that increases the turnover of GABA, arginine and/or tryptophan leading to a reduced level of production of serotonin, GABA or nitric oxide for a given precursor blood level. Research has also shown that a genetic predisposition to accelerated degradation can lead to increased precursor requirements in certain patients with pain disorders and inflammatory conditions. Choline is required to fully potentiate acetylcholine synthesis by brain neurons. A deficiency of choline leads to reduced acetylcholine production by the neurons. Flavonoids potentiate the production of acetylcholine by the neurons thereby reducing delta pain. Diets deficient in flavonoid rich foods and choline result in inadequate flavonoid concentrations, impeding acetylcholine production in certain patients with pain disorders and/or inflammatory conditions. Acetylcholine in pre-synaptic ganglia is necessary for the production of serotonin and nitric oxide in post-synaptic ganglia. Provision of tryptophan, arginine, GABA, choline and flavonoids with antioxidants, in specific proportions can restore the production of beneficial serotonin, nitric oxide, and acetylcholine, thereby reducing the perception of pain and reducing inflammation. L-Histidine is known to produce brain histamine that stimulates production of ACTH.

DESCRIPTION

PRODUCT DESCRIPTION Primary Ingredients Theramine consists of a proprietary blend of amino acids, cocoa, caffeine, cinnamon, and flavonoids in specific proportions. These ingredients fall into the category of Generally Regarded as Safe” (GRAS) as defined by the Food and Drug Administration (FDA) (Sections 201(s) and 409 of the Federal Food, Drug, and Cosmetic Act). A GRAS substance is distinguished from a food additive on the basis of the common knowledge about the safety of the substance for its intended use. The standard for an ingredient to achieve GRAS status requires not only technical demonstration of non-toxicity and safety, but also general recognition of safety through widespread usage and agreement of that safety by experts in the field. Many ingredients have been determined by the U.S. Food and Drug Administration (FDA) to be GRAS, and are listed as such by regulation, in Volume 21 Code of Federal Regulations (CFR) Sections 182, 184, and 186. Amino Acids Amino Acids are the building blocks of protein. All amino acids are GRAS listed as they have been ingested by humans for thousands of years. The doses of the amino acids in Theramine are equivalent to those found in the usual human diet. Patients with pain disorders may require an increased amount of certain amino acids that cannot be obtained from normal diet alone. Tryptophan, for example, is an obligatory amino acid. The body cannot make tryptophan and must obtain tryptophan from the diet. Tryptophan is needed to produce serotonin. Serotonin is required to reduce pain. Patients with pain disorders and inflammatory conditions have altered serotonin metabolism. Some patients with pain disorders and inflammatory conditions have a resistance to the use of tryptophan that is similar to the mechanism found in insulin resistance. Patients with pain disorders and inflammatory conditions cannot acquire sufficient tryptophan from the diet to alter the perception of pain and the inflammatory process without ingesting a prohibitively large amount of calories, particularly calories from protein. Flavonoids Flavonoids are a group of phytochemical compounds found in all vascular plants including fruits and vegetables. They are a part of a larger class of compounds known as polyphenols. Many of the therapeutic or health benefits of colored fruits and vegetables, cocoa, red wine, and green tea are directly related to their flavonoid content. The specially formulated flavonoids found in Theramine cannot be obtained from conventional foods in the necessary proportions to elicit a therapeutic response. Other Ingredients Theramine contains the following inactive or other ingredients, as fillers, excipients, and colorings: magnesium stearate, microcrystalline cellulose, Maltodextrin NF, gelatin (as the capsule material). Physical Description Theramine is a yellow to light brown powder. Theramine contains L-Glutamine, L-Arginine, L-Histidine, and L-Serine, 5-Hydroxytryptophan as Griffonia Seed Extract, GABA, Choline Bitartrate, Cinnamon, Cocoa, Hydrolyzed Whey Protein, and Grape Seed Extract.

CLINICAL PHARMACOLOGY

CLINICAL PHARMACOLOGY Mechanism of Action Theramine acts by restoring and maintaining the balance of the neurotransmitters; GABA, nitric oxide, serotonin, and acetylcholine that are associated with pain disorders and inflammatory conditions. Theramine stimulates the production ACTH to reduce inflammation. Metabolism The amino acids in Theramine are primarily absorbed by the stomach and small intestines. All cells metabolize the amino acids in Theramine. Circulating tryptophan, arginine and choline blood levels determine the production of serotonin, nitric oxide, and acetylcholine. Excretion Theramine is not an inhibitor of cytochrome P450 1A2, 2C9, 2C19, 2D6, or 3A4. These isoenzymes are principally responsible for 95% of all detoxification of drugs, with CYP3A4 being responsible for detoxification of roughly 50% of drugs. Amino acids do not appear to have an effect on drug metabolizing enzymes.

INDICATIONS AND USAGE

INDICATIONS FOR USE Theramine is intended for the clinical dietary management of the metabolic processes of pain disorders and inflammatory conditions.

CLINICAL STUDIES

CLINICAL EXPERIENCE Administration of Theramine has demonstrated significant reduction in symptoms of pain and inflammation in patients with acute and chronic pain when used for the dietary management of the metabolic processes associated with pain disorders and inflammatory conditions. Administration of Theramine results in the induction and maintenance of pain relief in patients with pain disorders and inflammatory conditions.

CONTRAINDICATIONS

PRECAUTIONS AND CONTRAINDICATIONS Theramine is contraindicated in an extremely small number of patients with hypersensitivity to any of the nutritional components of Theramine.

ADVERSE REACTIONS

ADVERSE REACTIONS Oral supplementation with L-tryptophan, L-arginine or choline at high doses up to 15 grams daily is generally well tolerated. The most common adverse reactions of higher doses — from 15 to 30 grams daily — are nausea, abdominal cramps, and diarrhea. Some patients may experience these symptoms at lower doses. The total combined amount of amino acids in each Theramine capsule does not exceed 400 mg.

DRUG INTERACTIONS

DRUG INTERACTIONS Theramine does not directly influence the pharmacokinetics of prescription drugs. Clinical experience has shown that administration of Theramine may allow for lowering the dose of co-administered drugs under physician supervision.

OVERDOSAGE

OVERDOSE There is a negligible risk of overdose with Theramine as the total dosage of amino acids in a one month supply (90 capsules) is less than 36 grams. Overdose symptoms may include diarrhea, weakness, and nausea. POST-MARKETING SURVEILLANCE Post-marketing surveillance has shown no serious adverse reactions. Reported cases of mild rash and itching may have been associated with allergies to Theramine flavonoid ingredients, including cinnamon, cocoa, and chocolate. These reactions were transient in nature and subsided within 24 hours.

DOSAGE AND ADMINISTRATION Recommended Administration For the dietary management of the metabolic processes associated with pain disorders and inflammatory conditions. Take (2) capsules one to three times daily or as directed by physician. As with most amino acid formulations Theramine should be taken without food to increase the absorption of key ingredients.

HOW SUPPLIED

How Supplied Theramine is supplied in purple and white, size 0 capsules in bottles of 60 or 90 capsules. Physician Supervision Theramine is a Medical Food product available by prescription only and must be used while the patient is under ongoing physician supervision. U.S. patent pending. Manufactured by Arizona Nutritional Supplements, Inc. Chandler AZ 85225 Distributed by Physician Therapeutics LLC, Los Angeles, CA 90077. www.ptlcentral.com Copyright 2003-2006, Physician Therapeutics LLC, all rights reserved NDC: 68405-1008-02 NDC: 68405-1008-03

STORAGE AND HANDLING

Storage Store at room temperature, 59-86OF (15-30OC) Protect from light and moisture. Theramine is supplied to physicians in a recyclable plastic bottle with a child-resistant cap.

PACKAGE LABEL

PHYSICIAN THERAPEUTICS THERAMINE Medical Food Rx only 60 Capsules Directions for use: Must be administered under medical supervision. For adults only. As a Medical Food, take one (1) or two (2) capsules every four hours or as directed by your medical practitioner. For the dietary management of Myalgia. Contains no added sugar, starch, wheat, yeast, preservatives, artificial flavor. Storage: Keep tightly closed in a cool dry place 8-320 C (45-900 F), relative humidity, below 50%. Warning: Keep this product out of the reach of children. NDC# 68405-1008-02 Ingredients: Each serving (per 2 capsules) contains: Proprietary Amino Acid Blend Griffonia Seed Extract (5-HTP), Whey Protein Hydrolysate, L-Arginini, L-Histidine (as L-Histidine HCl), L-Glutamine, L-Serine, Gamma Amino Butyric Acid, Choline Bitartrate, Cocoa (6% Theobromine) (fruit), Grape Extract (95% Polyphenols) (seed), Cinnamon (bark) Other Ingredients: Gelatin, Silicon Dioxide, Tricalcium phosphate, Vegetable Magnesium Stearate, Cellulose, FD and C Blue #1, FD and C red#3, titanium dioxide. Distributed by: Physician Therapeutics LLC, Los Angeles, CA 90077 www.ptlcentral.com Patent Pending

PACKAGE LABEL

Fot the Dietary Management of Pain and Inflammation. Two capsules twice daily or as directed by physician. See product label and insert. Theramine Medical Food A Convenience Packed Medical Food And Drug Therafeldamine PHYSICIAN THERAPEUTICS - Theramine 60 Capsules- Piroxicam 20 mg 30 Capsules Rx Only NDC# 68405-8078-26 of this co-pack No Refills Without Physician Authorization FRONT VIEW As prescribed by physician. See product label and product information insert. Piroxicam 20 mg Rx Drug 68405-8078-26 BACK VIEW Physician Therapeutics LLC Los Angeles, CA 90077 on November 21, 2006